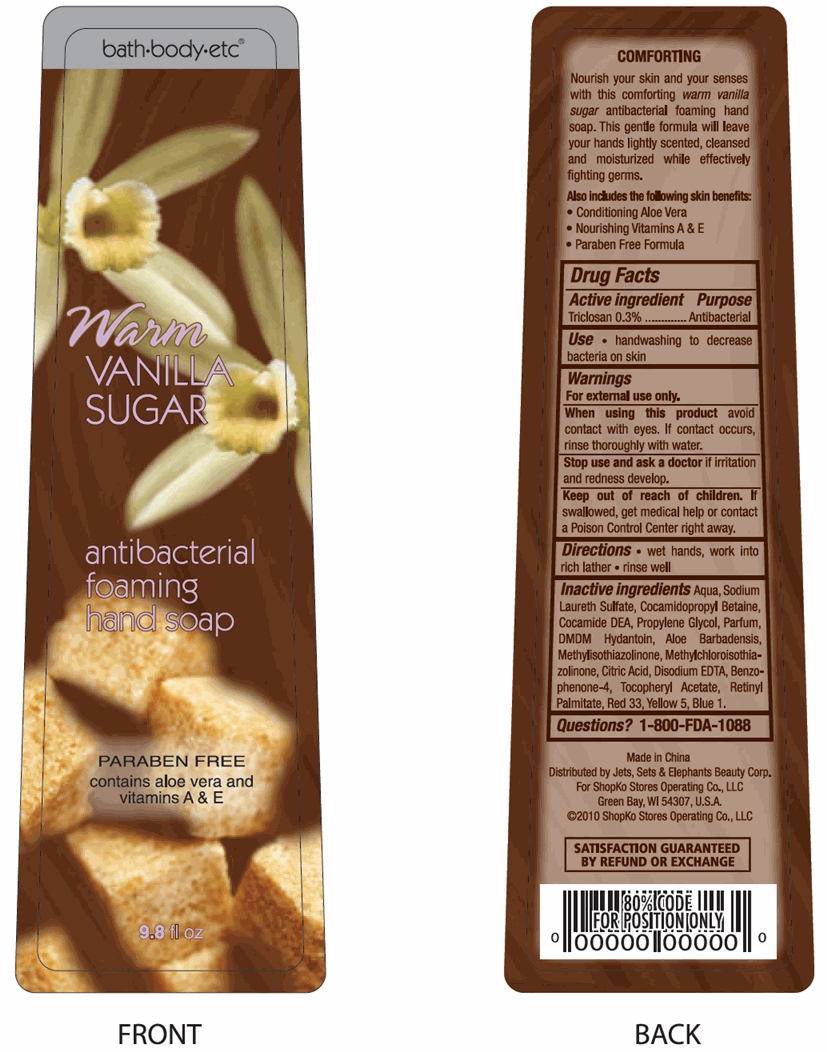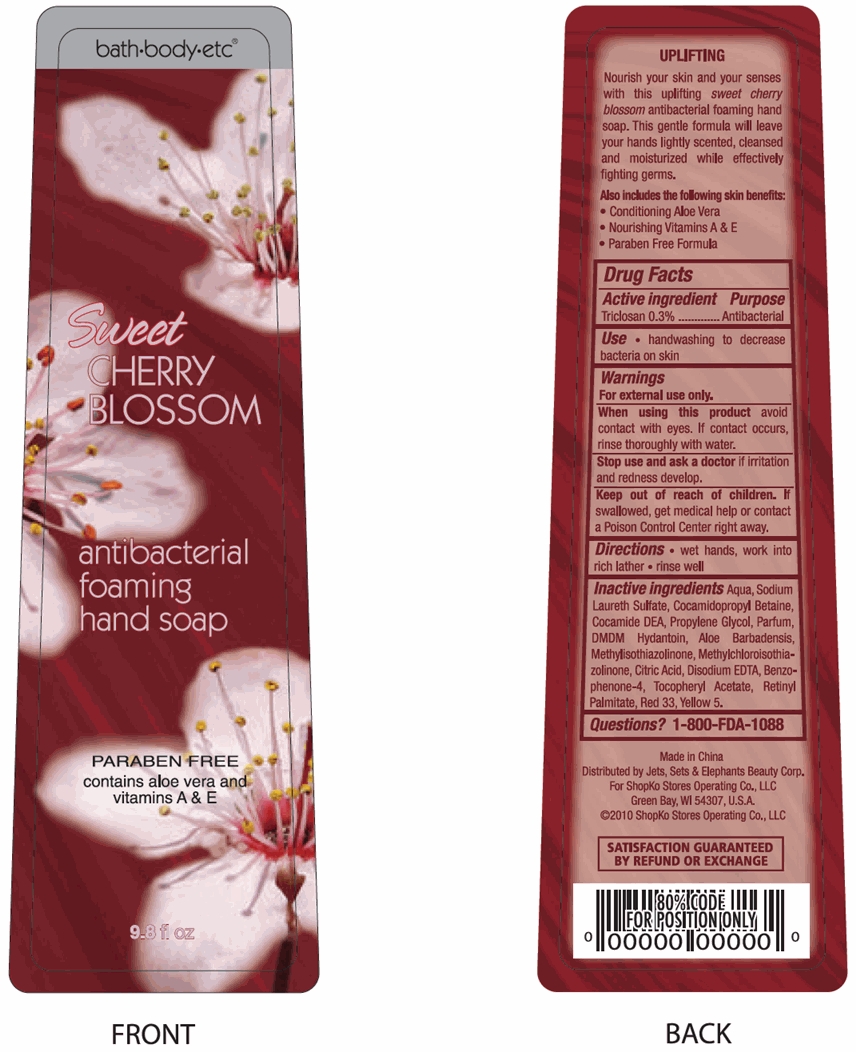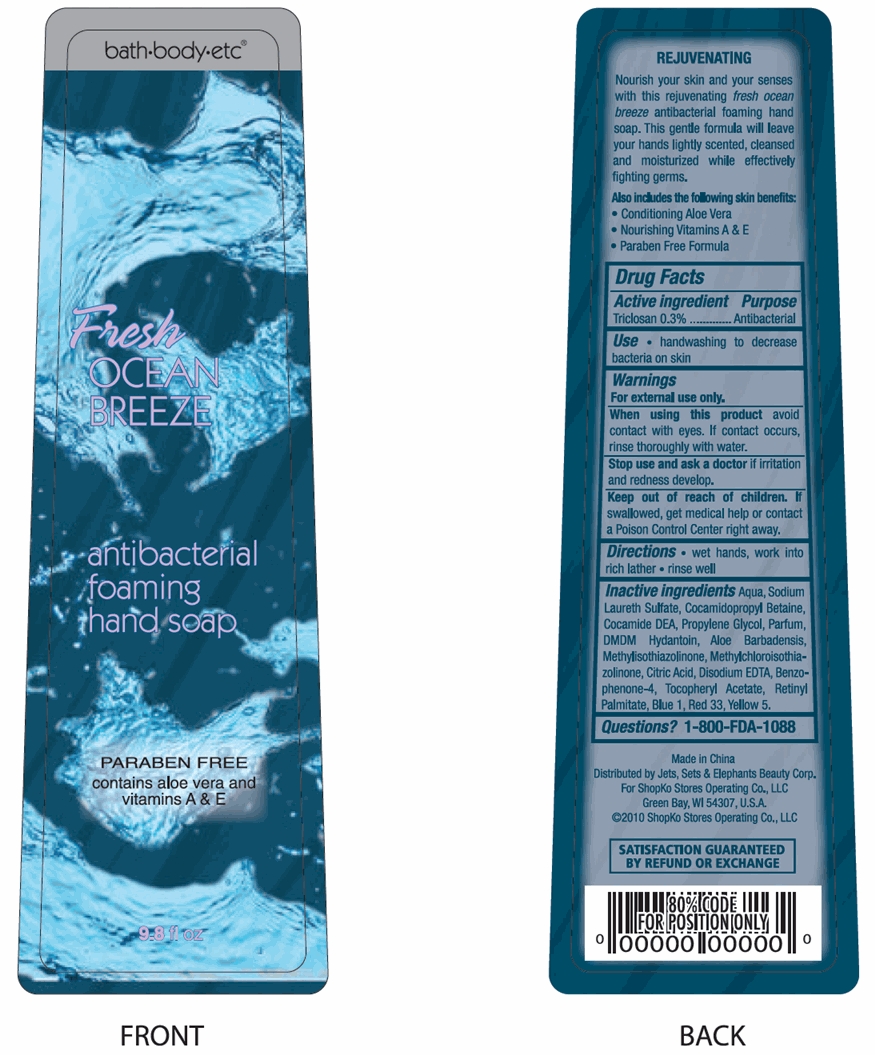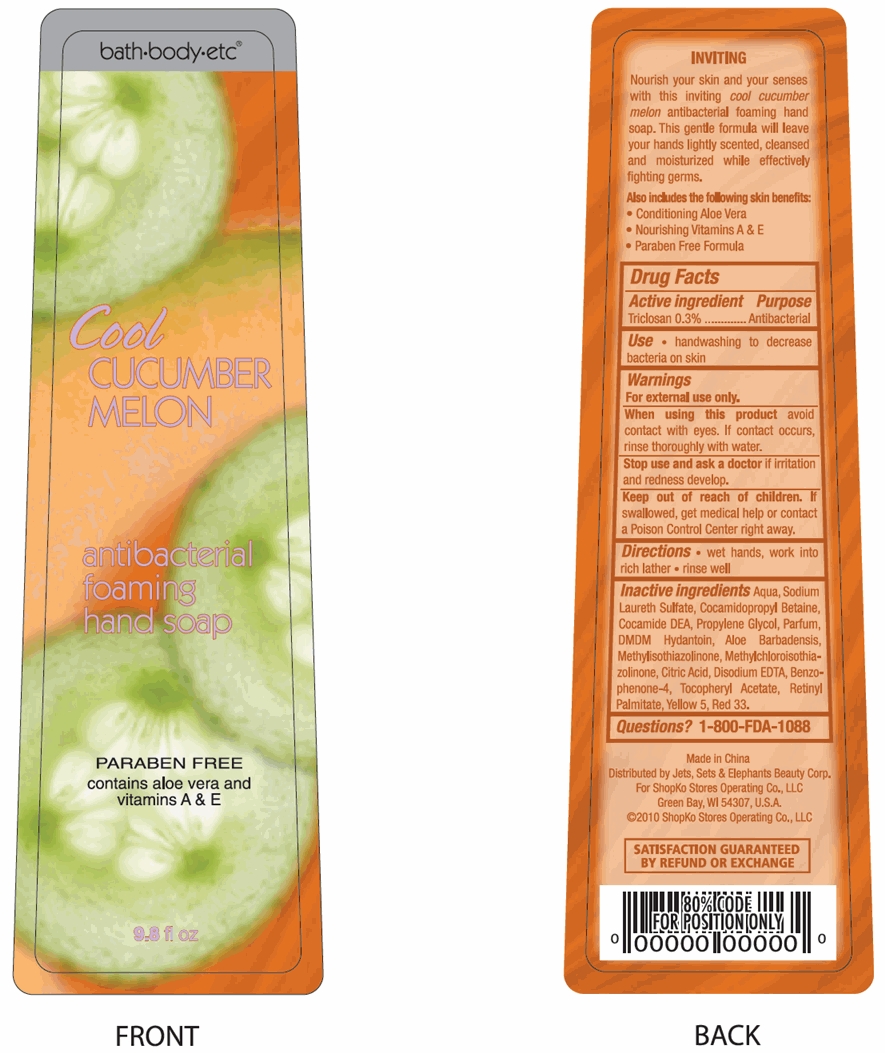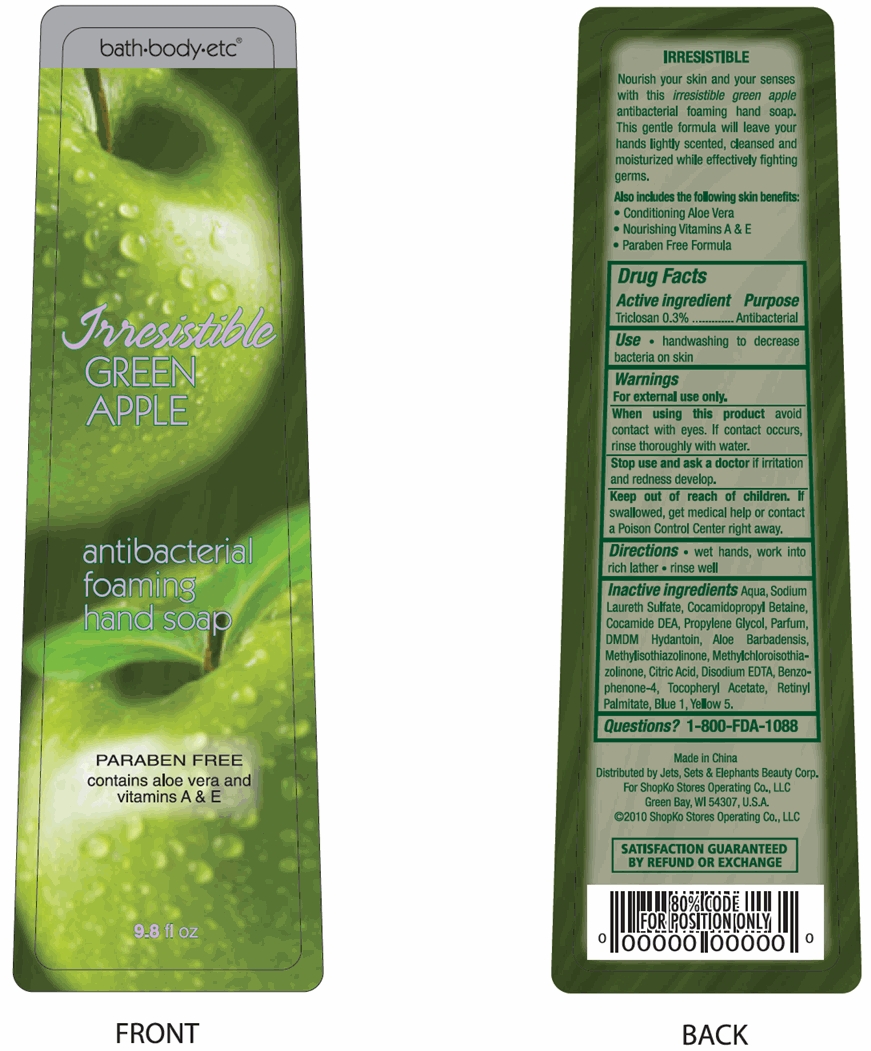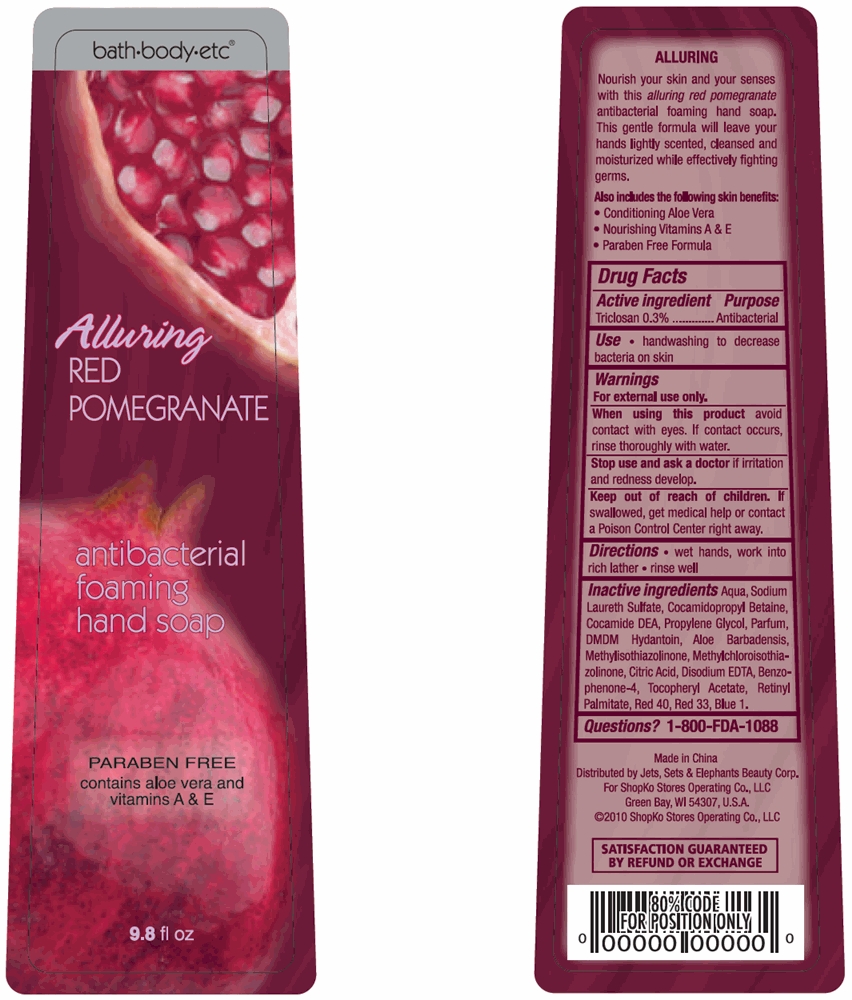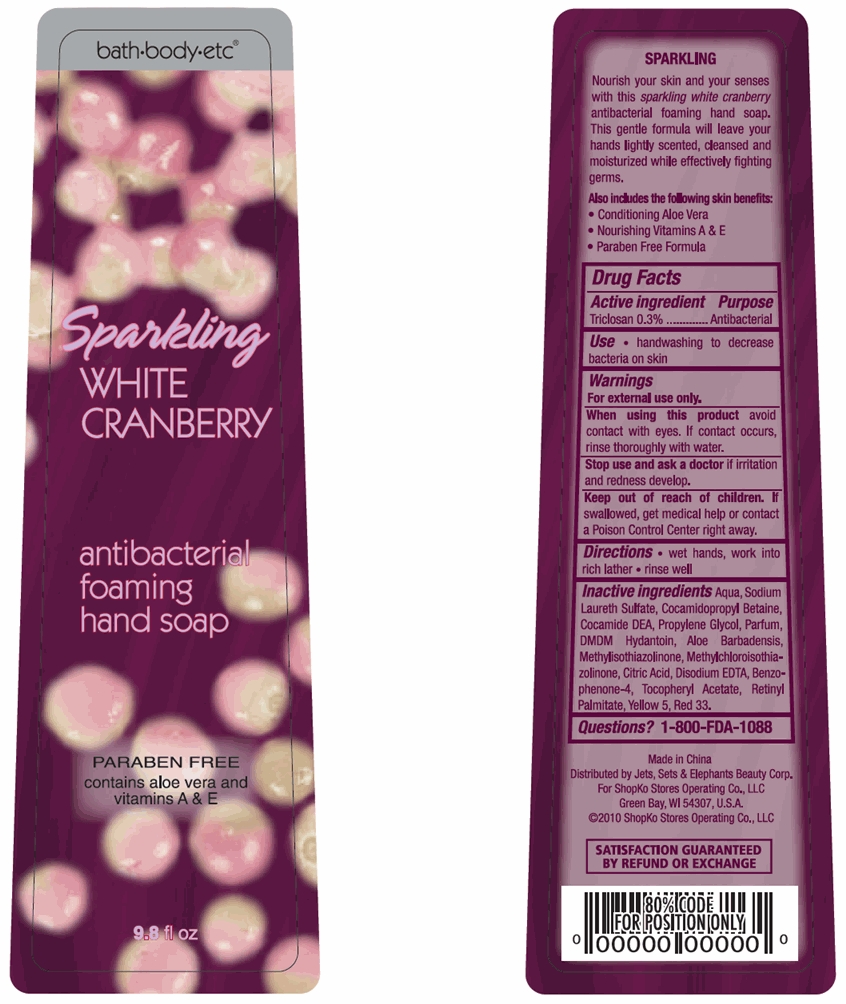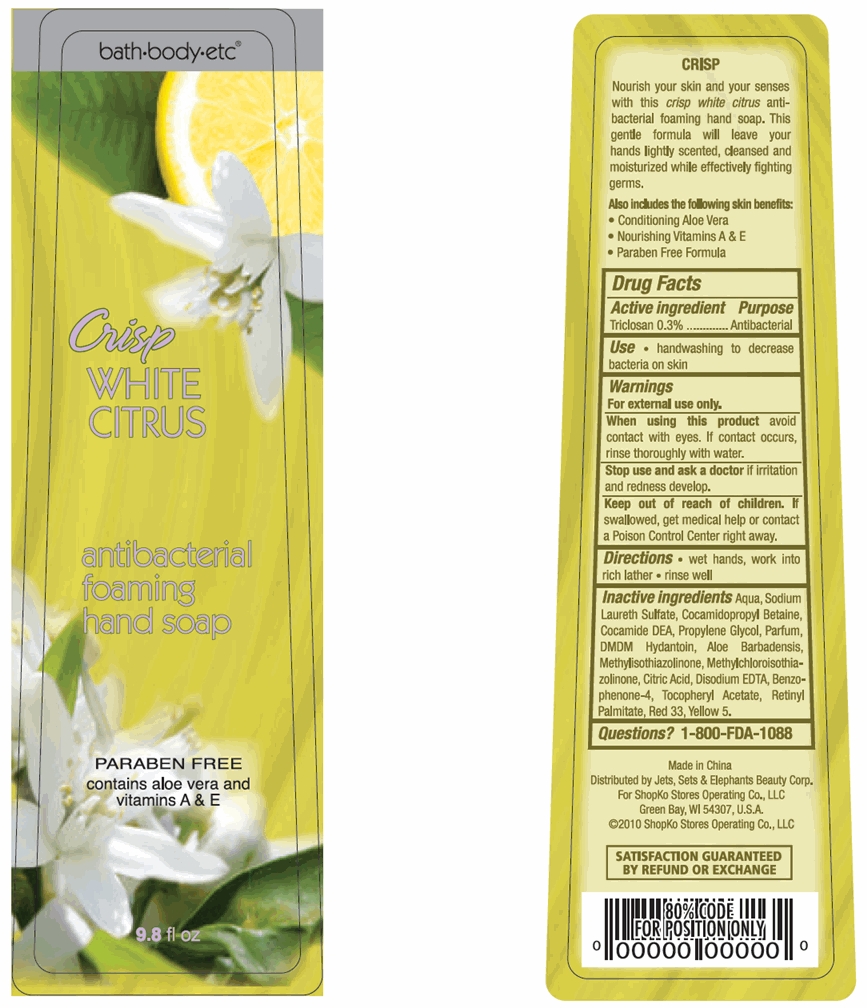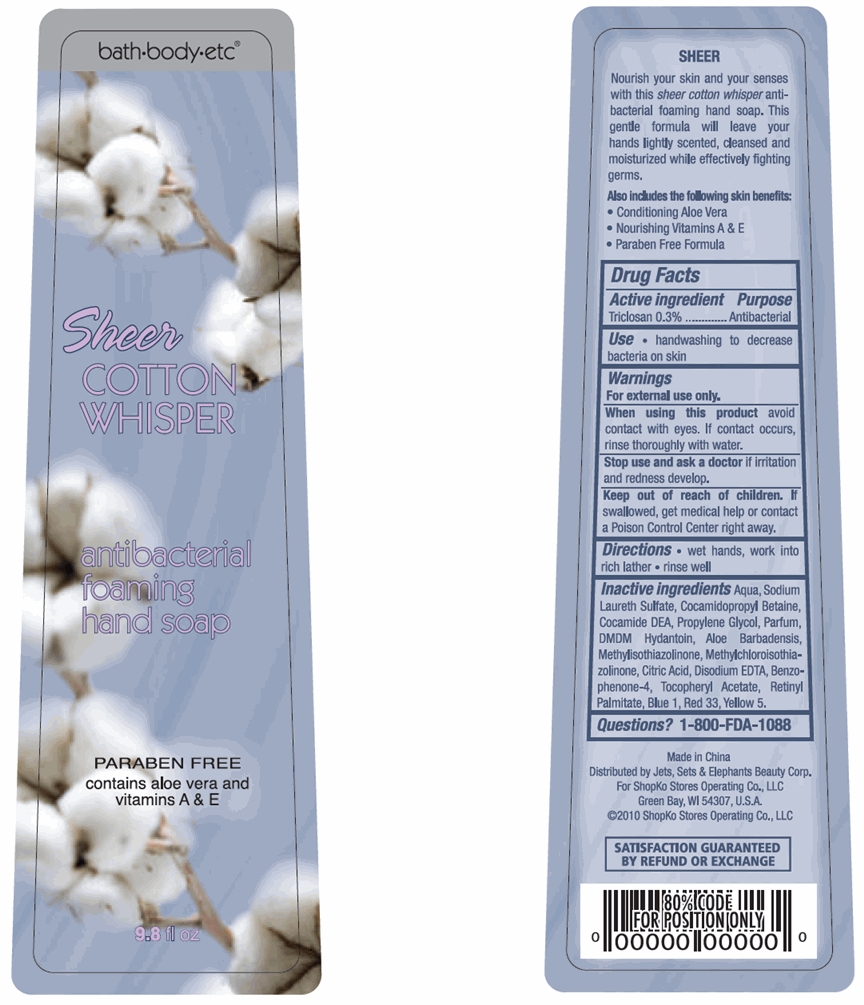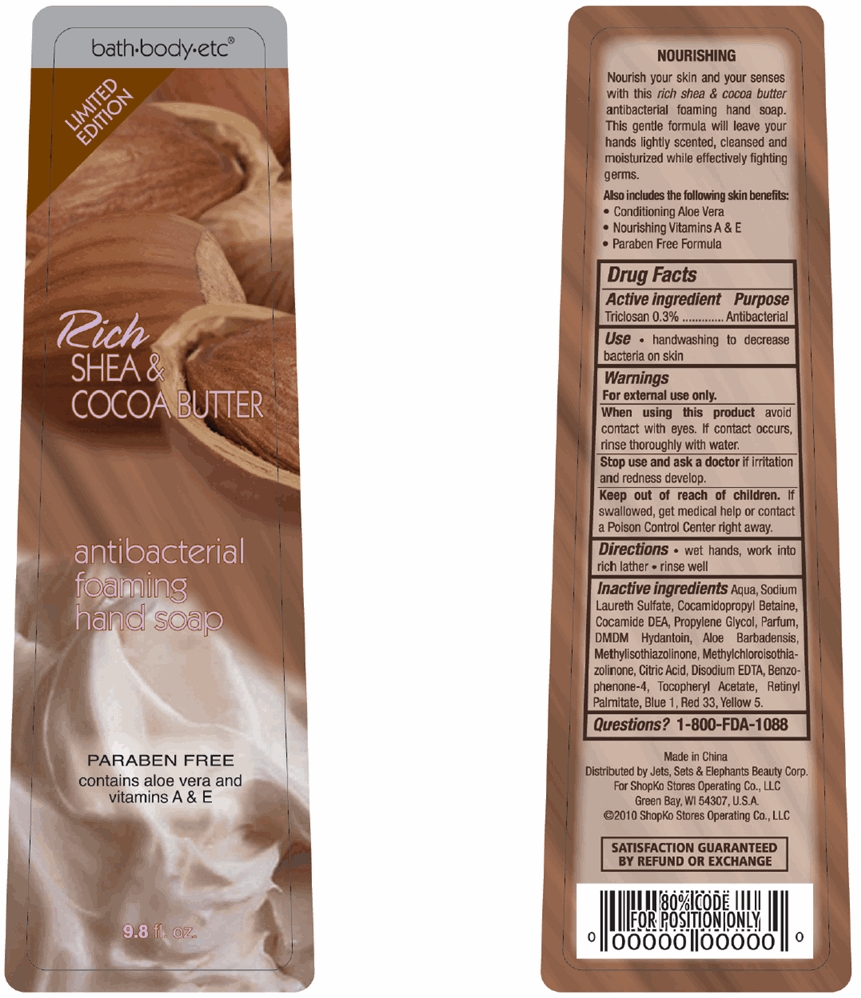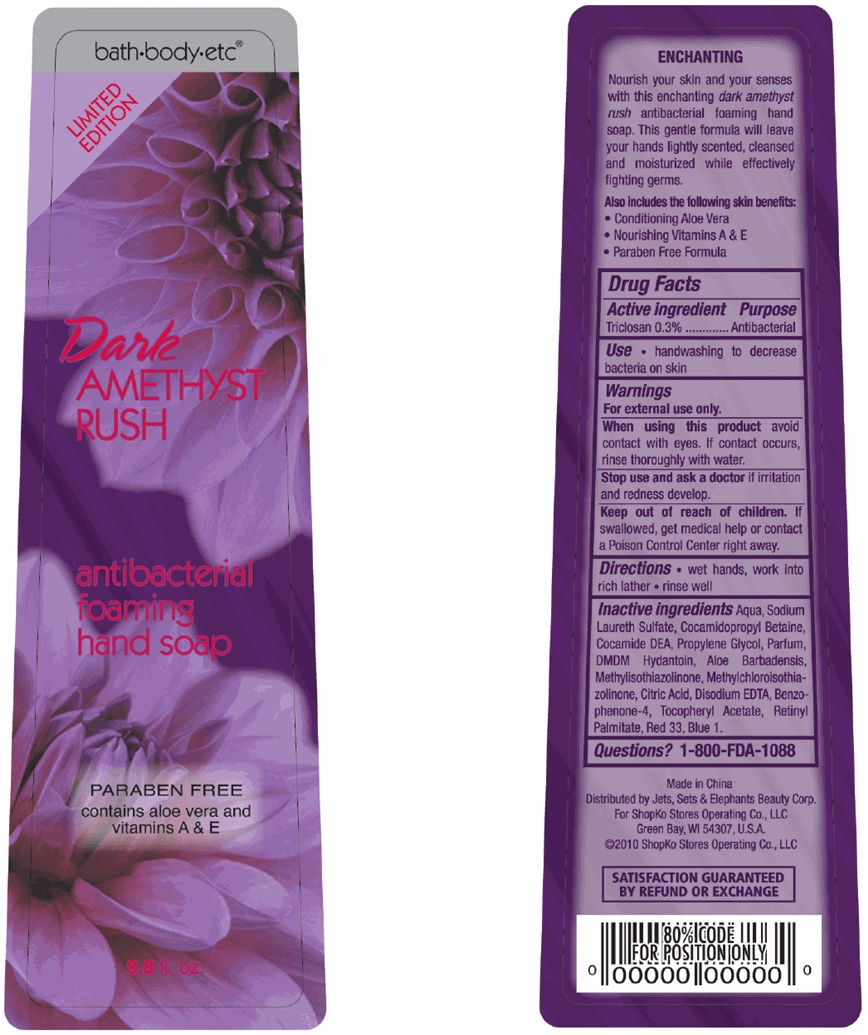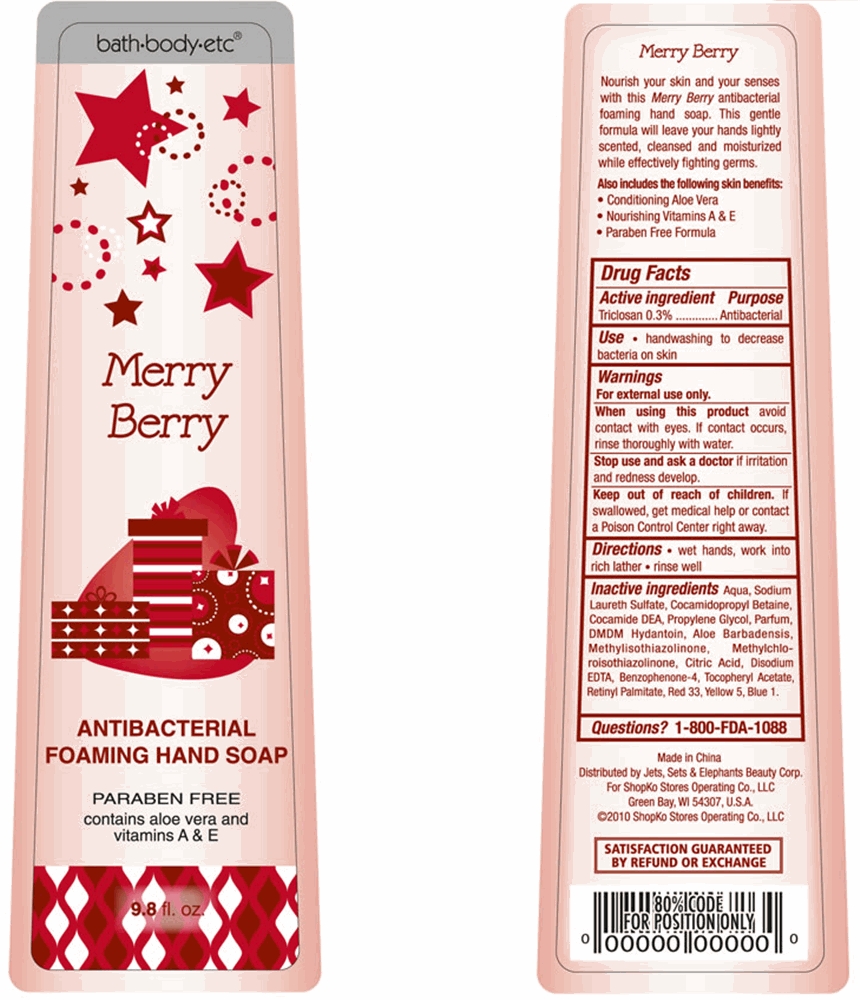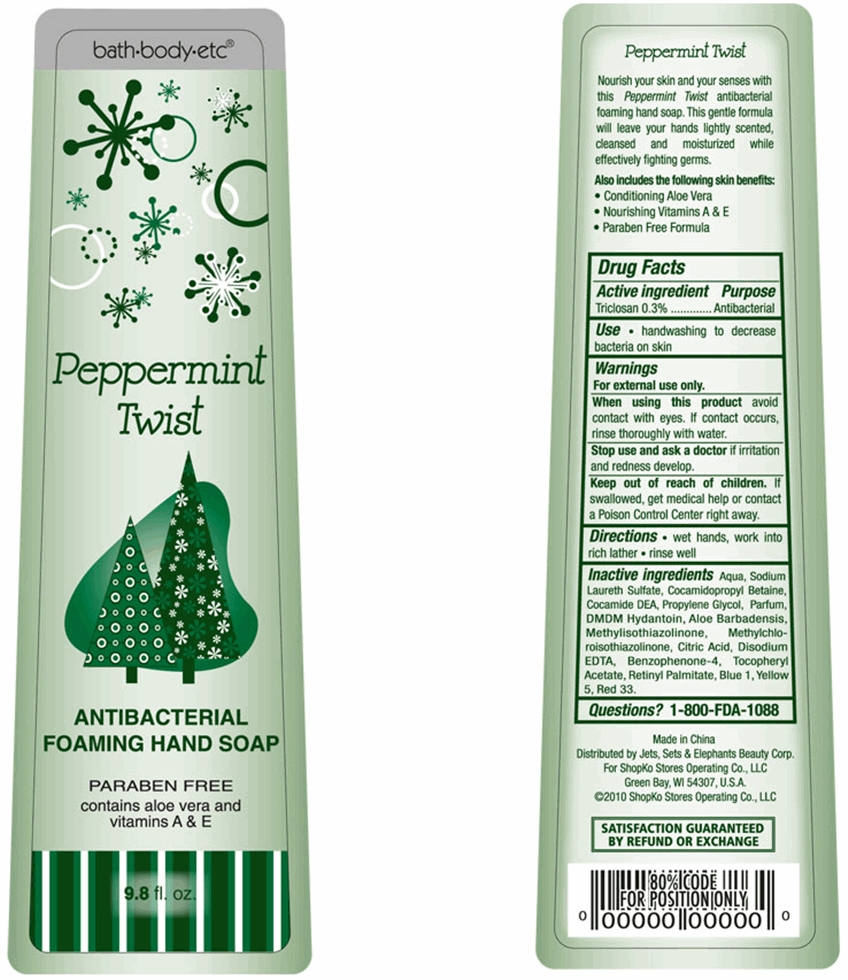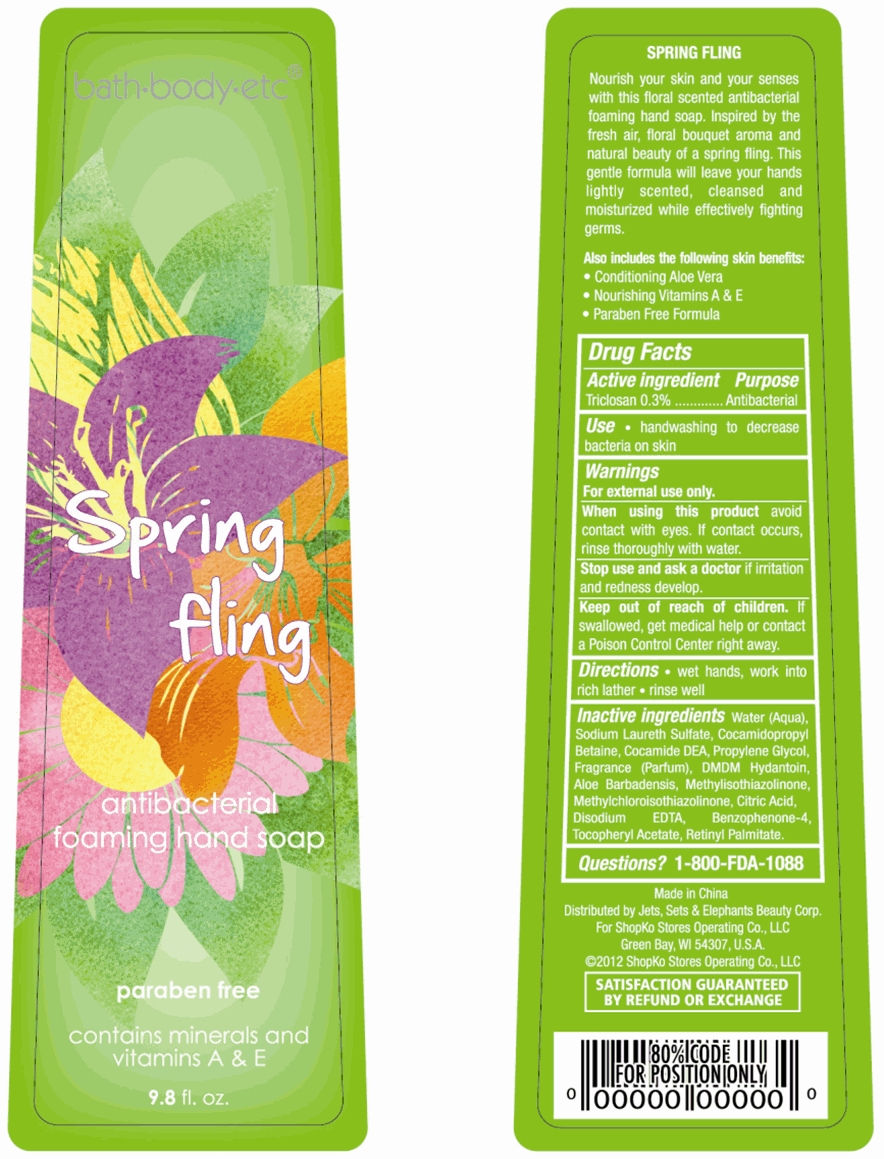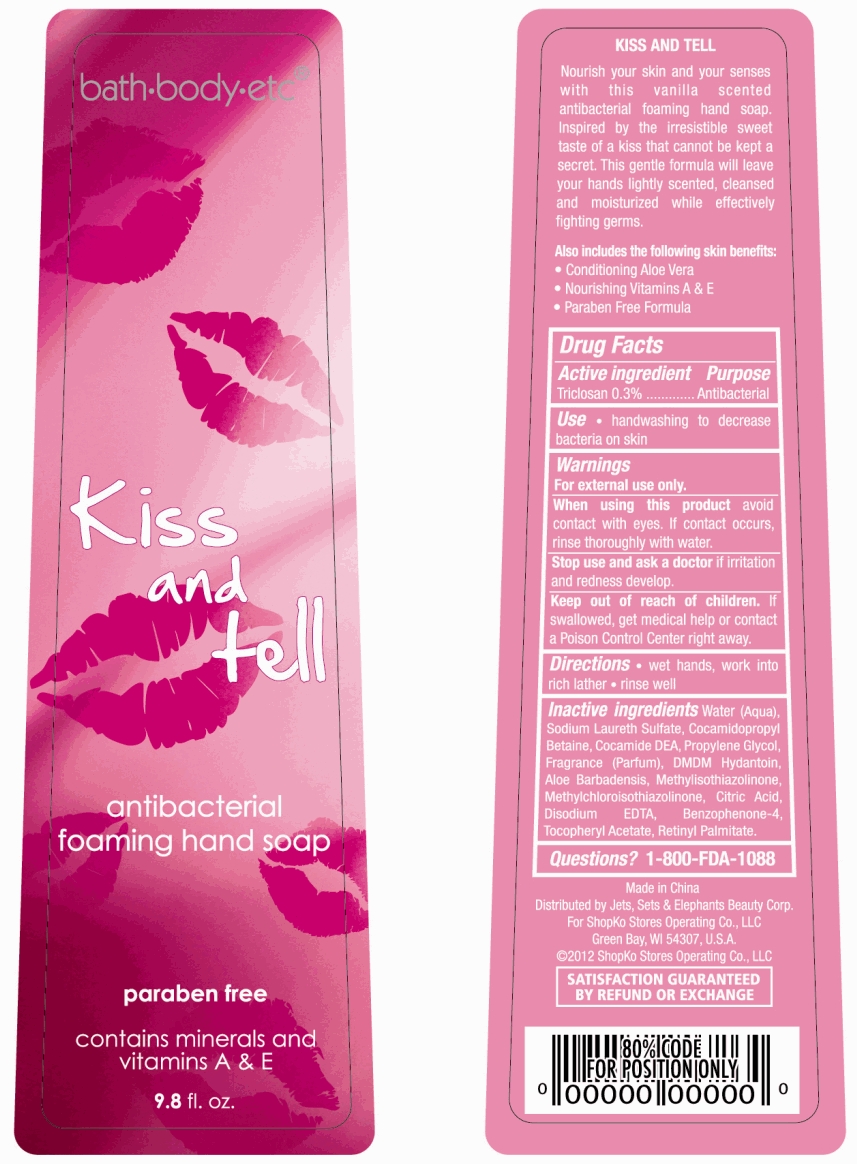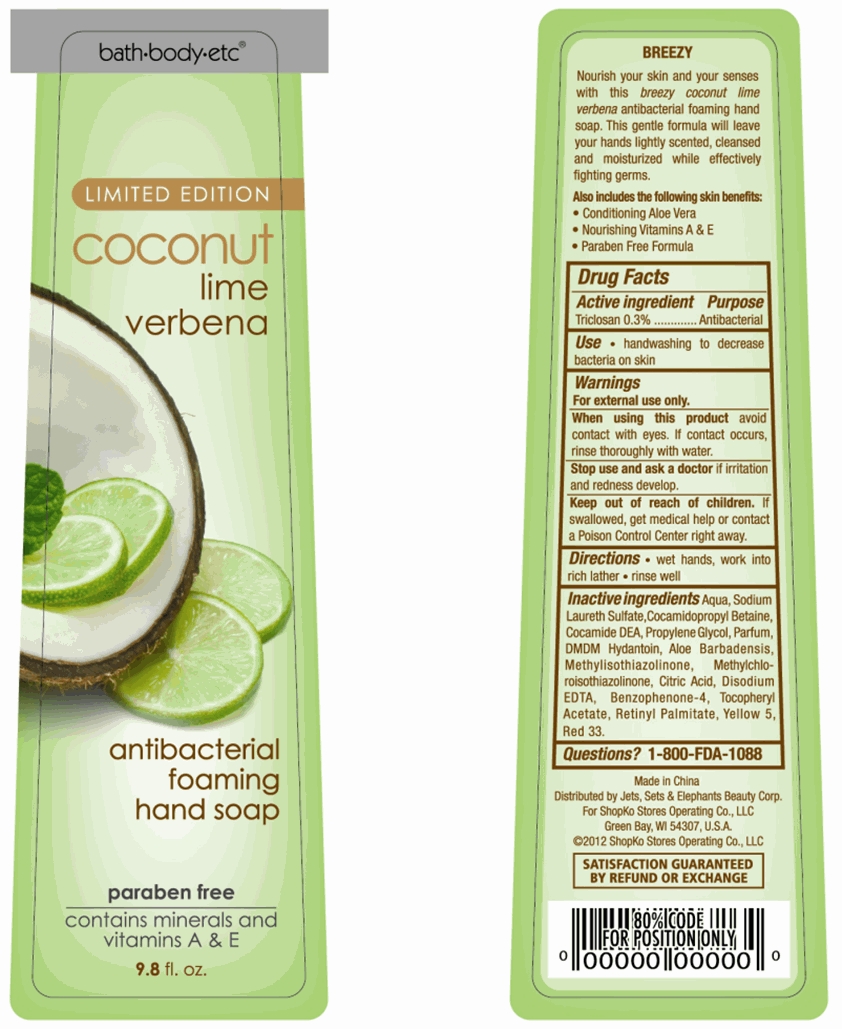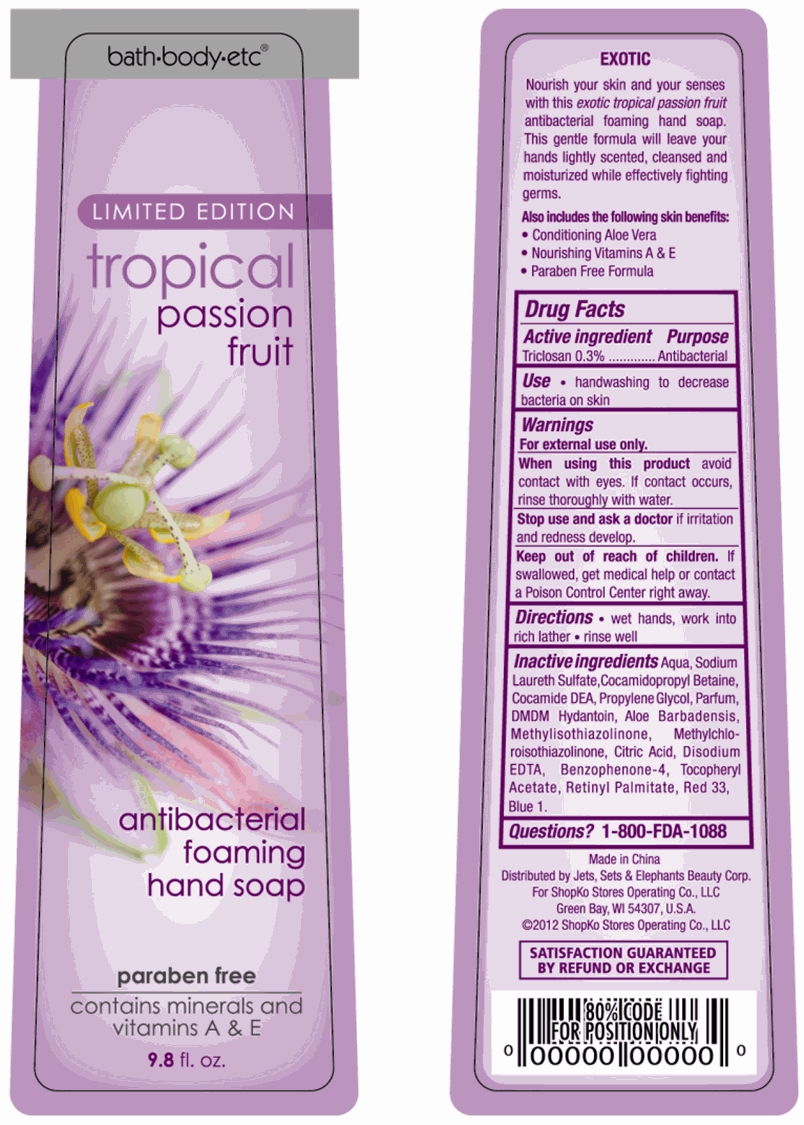 DRUG LABEL: Antibacterial Foaming Hand Cleanser
NDC: 50988-170 | Form: SOLUTION
Manufacturer: Jets, Sets, & Elephants Beauty Corp.
Category: otc | Type: HUMAN OTC DRUG LABEL
Date: 20111201

ACTIVE INGREDIENTS: TRICLOSAN 0.869 mL/289.82 mL
INACTIVE INGREDIENTS: WATER; SODIUM LAURETH SULFATE; COCAMIDOPROPYL BETAINE; COCO DIETHANOLAMIDE; PROPYLENE GLYCOL; DMDM HYDANTOIN; ALOE VERA LEAF; METHYLISOTHIAZOLINONE; METHYLCHLOROISOTHIAZOLINONE; CITRIC ACID MONOHYDRATE; EDETATE DISODIUM; SULISOBENZONE; .ALPHA.-TOCOPHEROL ACETATE, D-; VITAMIN A PALMITATE; D&C RED NO. 33; FD&C BLUE NO. 1; FD&C YELLOW NO. 5

bath+body+etc® antibacterial foaming hand soap - Warm Vanilla Sugar, Sweet Cherry Blossom, Fresh Ocean Breeze, Cool Cucumber Melon, Irresistible Green Apple, Alluring Red Pomegranate, Sparkling White Cranberry, Crisp White Citrus, Sheer Cotton Whisper, Rich Shea & Cocoa Butter, Dark Amethyst Rush, Merry Berry, Peppermint Twist, Spring Fling, Kiss and Tell, Coconut Lime Verbena, Tropical Passion Fruit

Active ingredient

Triclosan 0.3%

Purpose

Antibacterial

Uses

- handwashing to decrease bacteria on skin

Warnings

For external use only.

When using this product avoid contact with eyes. If contact occurs, rinse thoroughly with water.

Stop use and ask a doctor if irritation and redness develop.

Keep out of reach of children.

If swallowed, get medical help or contact a Poison Control Center right away.

Directions

- wet hands, work into rich lather
- rinse well

Inactive Ingredients

Warm Vanilla Sugar

Aqua, Sodium Laureth Sulfate, Cocamidopropyl Betaine, Cocamide DEA, Propylene Glycol, Parfum, DMDM Hydantoin, Aloe Barbadensis, Methylisothiazolinone, Methylchloroisothiazolinone, Citric Acid, Disodium EDTA, Benzophenone-4, Tocopheryl Acetate, Retinyl Palmitate, Red 33, Blue 1, Yellow 5

Sweet Cherry Blossom

Aqua, Sodium Laureth Sulfate, Cocamidopropyl Betaine, Cocamide DEA, Propylene Glycol, Parfum, DMDM Hydantoin, Aloe Barbadensis, Methylisothiazolinone, Methylchloroisothiazolinone, Citric Acid, Disodium EDTA, Benzophenone-4, Tocopheryl Acetate, Retinyl Palmitate, Red 33, Yellow 5

Fresh Ocean Breeze

Aqua, Sodium Laureth Sulfate, Cocamidopropyl Betaine, Cocamide DEA, Propylene Glycol, Parfum, DMDM Hydantoin, Aloe Barbadensis, Methylisothiazolinone, Methylchloroisothiazolinone, Citric Acid, Disodium EDTA, Benzophenone-4, Tocopheryl Acetate, Retinyl Palmitate, Red 33, Blue 1, Yellow 5

Cool Cucumber Melon

Aqua, Sodium Laureth Sulfate, Cocamidopropyl Betaine, Cocamide DEA, Propylene Glycol, Parfum, DMDM Hydantoin, Aloe Barbadensis, Methylisothiazolinone, Methylchloroisothiazolinone, Citric Acid, Disodium EDTA, Benzophenone-4, Tocopheryl Acetate, Retinyl Palmitate, Red 33, Yellow 5

Irresistible Green Apple

Aqua, Sodium Laureth Sulfate, Cocamidopropyl Betaine, Cocamide DEA, Propylene Glycol, Parfum, DMDM Hydantoin, Aloe Barbadensis, Methylisothiazolinone, Methylchloroisothiazolinone, Citric Acid, Disodium EDTA, Benzophenone-4, Tocopheryl Acetate, Retinyl Palmitate, Blue 1, Yellow 5

Alluring Red Pomegranate

Aqua, Sodium Laureth Sulfate, Cocamidopropyl Betaine, Cocamide DEA, Propylene Glycol, Parfum, DMDM Hydantoin, Aloe Barbadensis, Methylisothiazolinone, Methylchloroisothiazolinone, Citric Acid, Disodium EDTA, Benzophenone-4, Tocopheryl Acetate, Retinyl Palmitate, Red 40, Red 33, Blue 1

Sparkling White Cranberry

Aqua, Sodium Laureth Sulfate, Cocamidopropyl Betaine, Cocamide DEA, Propylene Glycol, Parfum, DMDM Hydantoin, Aloe Barbadensis, Methylisothiazolinone, Methylchloroisothiazolinone, Citric Acid, Disodium EDTA, Benzophenone-4, Tocopheryl Acetate, Retinyl Palmitate, Red 33, Yellow 5

Crisp White Citrus

Aqua, Sodium Laureth Sulfate, Cocamidopropyl Betaine, Cocamide DEA, Propylene Glycol, Parfum, DMDM Hydantoin, Aloe Barbadensis, Methylisothiazolinone, Methylchloroisothiazolinone, Citric Acid, Disodium EDTA, Benzophenone-4, Tocopheryl Acetate, Retinyl Palmitate, Red 33, Yellow 5

Sheer Cotton Whisper

Aqua, Sodium Laureth Sulfate, Cocamidopropyl Betaine, Cocamide DEA, Propylene Glycol, Parfum, DMDM Hydantoin, Aloe Barbadensis, Methylisothiazolinone, Methylchloroisothiazolinone, Citric Acid, Disodium EDTA, Benzophenone-4, Tocopheryl Acetate, Retinyl Palmitate, Blue 1, Red 33, Yellow 5

Rich Shea & Cocoa Butter

Aqua, Sodium Laureth Sulfate, Cocamidopropyl Betaine, Cocamide DEA, Propylene Glycol, Parfum, DMDM Hydantoin, Aloe Barbadensis, Methylisothiazolinone, Methylchloroisothiazolinone, Citric Acid, Disodium EDTA, Benzophenone-4, Tocopheryl Acetate, Retinyl Palmitate, Blue 1, Red 33, Yellow 5

Dark Amethyst Rush

Aqua, Sodium Laureth Sulfate, Cocamidopropyl Betaine, Cocamide DEA, Propylene Glycol, Parfum, DMDM Hydantoin, Aloe Barbadensis, Methylisothiazolinone, Methylchloroisothiazolinone, Citric Acid, Disodium EDTA, Benzophenone-4, Tocopheryl Acetate, Retinyl Palmitate, Red 33, Blue 1

Merry Berry

Aqua, Sodium Laureth Sulfate, Cocamidopropyl Betaine, Cocamide DEA, Propylene Glycol, Parfum, DMDM Hydantoin, Aloe Barbadensis, Methylisothiazolinone, Methylchloroisothiazolinone, Citric Acid, Disodium EDTA, Benzophenone-4, Tocopheryl Acetate, Retinyl Palmitate, Red 33, Yellow 5, Blue 1

Peppermint Twist

Aqua, Sodium Laureth Sulfate, Cocamidopropyl Betaine, Cocamide DEA, Propylene Glycol, Parfum, DMDM Hydantoin, Aloe Barbadensis, Methylisothiazolinone, Methylchloroisothiazolinone, Citric Acid, Disodium EDTA, Benzophenone-4, Tocopheryl Acetate, Retinyl Palmitate, Blue 1, Yellow 5, Red 33

Spring Fling

Aqua, Sodium Laureth Sulfate, Cocamidopropyl Betaine, Cocamide DEA, Propylene Glycol, Parfum, DMDM Hydantoin, Aloe Barbadensis, Methylisothiazolinone, Methylchloroisothiazolinone, Citric Acid, Disodium EDTA, Benzophenone-4, Tocopheryl Acetate, Retinyl Palmitate

Kiss and Tell

Aqua, Sodium Laureth Sulfate, Cocamidopropyl Betaine, Cocamide DEA, Propylene Glycol, Parfum, DMDM Hydantoin, Aloe Barbadensis, Methylisothiazolinone, Methylchloroisothiazolinone, Citric Acid, Disodium EDTA, Benzophenone-4, Tocopheryl Acetate, Retinyl Palmitate

Coconut Lime Verbena

Aqua, Sodium Laureth Sulfate, Cocamidopropyl Betaine, Cocamide DEA, Propylene Glycol, Parfum, DMDM Hydantoin, Aloe Barbadensis, Methylisothiazolinone, Methylchloroisothiazolinone, Citric Acid, Disodium EDTA, Benzophenone-4, Tocopheryl Acetate, Retinyl Palmitate, Red 33, Yellow 5

Tropical Passion Fruit

Aqua, Sodium Laureth Sulfate, Cocamidopropyl Betaine, Cocamide DEA, Propylene Glycol, Parfum, DMDM Hydantoin, Aloe Barbadensis, Methylisothiazolinone, Methylchloroisothiazolinone, Citric Acid, Disodium EDTA, Benzophenone-4, Tocopheryl Acetate, Retinyl Palmitate, Red 33, Blue 1

Questions?

1-800-FDA-1088

Made in China

Distributed by Jets, Sets & Elephants Beauty Corp.

For Shopko Stores Operating Co., LLC

Green Bay, WI 54307, U.S.A.

©2010 Shopko Stores Operating Co., LLC

Package/Label Principal Display Panel - Bottle Label

bath+body+etc®

Warm

VANILLA SUGAR

antibacterial

foaming

hand soap

PARABEN FREE

contains aloe vera and

vitamins A & E

9.8 fl oz

Warm Vanilla Sugar Bottle Label

Package/Label Principal Display Panel - Bottle Label

bath+body+etc®

Sweet

CHERRY BLOSSOM

antibacterial

foaming

hand soap

PARABEN FREE

contains aloe vera and

vitamins A & E

9.8 fl oz

Sweet Cherry Blossom Bottle Label

Package/Label Principal Display Panel - Bottle Label

bath+body+etc®

Fresh

OCEAN BREEZE

antibacterial

foaming

hand soap

PARABEN FREE

contains aloe vera and

vitamins A & E

9.8 fl oz

Fresh Ocean Breeze Bottle Label

Package/Label Principal Display Panel - Bottle Label

bath+body+etc®

Cool

CUCUMBER MELON

antibacterial

foaming

hand soap

PARABEN FREE

contains aloe vera and

vitamins A & E

9.8 fl oz

Cool Cucumber Melon Bottle Label

Package/Label Principal Display Panel - Bottle Label

bath+body+etc®

Irresistible

GREEN APPLE

antibacterial

foaming

hand soap

PARABEN FREE

contains aloe vera and

vitamins A & E

9.8 fl oz

Irresistible Green Apple Bottle Label

Package/Label Principal Display Panel - Bottle Label

bath+body+etc®

Alluring

RED POMEGRANATE

antibacterial

foaming

hand soap

PARABEN FREE

contains aloe vera and

vitamins A & E

9.8 fl oz

Alluring Red Pomegranate Bottle Label

Package/Label Principal Display Panel - Bottle Label

bath+body+etc®

Sparkling

WHITE CRANBERRY

antibacterial

foaming

hand soap

PARABEN FREE

contains aloe vera and

vitamins A & E

9.8 fl oz

Sparkling White Cranberry Bottle Label

Package/Label Principal Display Panel - Bottle Label

bath+body+etc®

Crisp

WHITE CITRUS

antibacterial

foaming

hand soap

PARABEN FREE

contains aloe vera and

vitamins A & E

9.8 fl oz

Crisp White Citrus Bottle Label

Package/Label Principal Display Panel - Bottle Label

bath+body+etc®

Sheer

COTTON WHISPER

antibacterial

foaming

hand soap

PARABEN FREE

contains aloe vera and

vitamins A & E

9.8 fl oz

Sheer Cotton Whisper Bottle Label

Package/Label Principal Display Panel - Bottle Label

bath+body+etc®

LIMITED EDITION

Rich

SHEA & COCOA BUTTER

antibacterial

foaming

hand soap

PARABEN FREE

contains aloe vera and

vitamins A & E

9.8 fl oz

Rich Shea & Cocoa Butter Bottle Label

Package/Label Principal Display Panel - Bottle Label

bath+body+etc®

LIMITED EDITION

Dark

AMETHYST RUSH

antibacterial

foaming

hand soap

PARABEN FREE

contains aloe vera and

vitamins A & E

9.8 fl oz

Dark Amethyst Rush Bottle Label

Package/Label Principal Display Panel - Bottle Label

bath+body+etc®

Merry Berry

Antibacterial

Foaming Hand Soap

PARABEN FREE

contains aloe vera and

vitamins A & E

9.8 fl oz

Merry Berry Bottle Label

Package/Label Principal Display Panel - Bottle Label

bath+body+etc®

Peppermint Twist

Antibacterial

Foaming Hand Soap

PARABEN FREE

contains aloe vera and

vitamins A & E

9.8 fl oz

Peppermint Twist Bottle Label

Package/Label Principal Display Panel - Bottle Label

bath+body+etc®

Spring Fling

antibacterial

foaming hand soap

paraben free

contains minerals and

vitamins A & E

9.8 fl oz

Spring Fling Bottle Label

Package/Label Principal Display Panel - Bottle Label

bath+body+etc®

Kiss and Tell

antibacterial

foaming hand soap

paraben free

contains minerals and

vitamins A & E

9.8 fl oz

Kiss and Tell Bottle Label

Package/Label Principal Display Panel - Bottle Label

bath+body+etc®

LIMITED EDITION

Coconut Lime Verbena

antibacterial

foaming hand soap

paraben free

contains minerals and

vitamins A & E

9.8 fl oz

Coconut Lime Verbena Bottle Label

Package/Label Principal Display Panel - Bottle Label

bath+body+etc®

LIMITED EDITION

Tropical Passion Fruit

antibacterial

foaming hand soap

paraben free

contains minerals and

vitamins A & E

9.8 fl oz

Tropical Passion Fruit Bottle Label